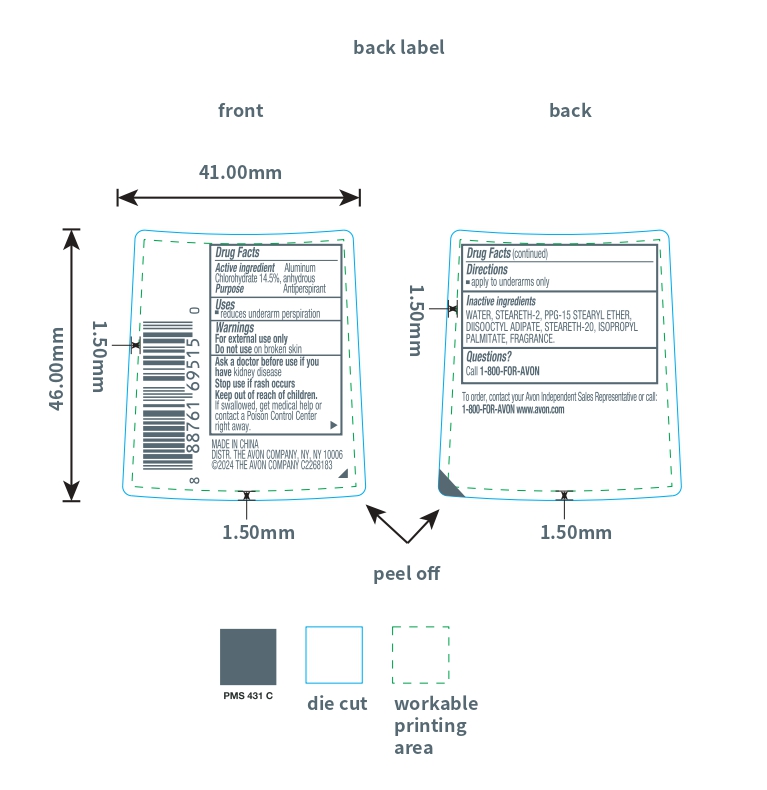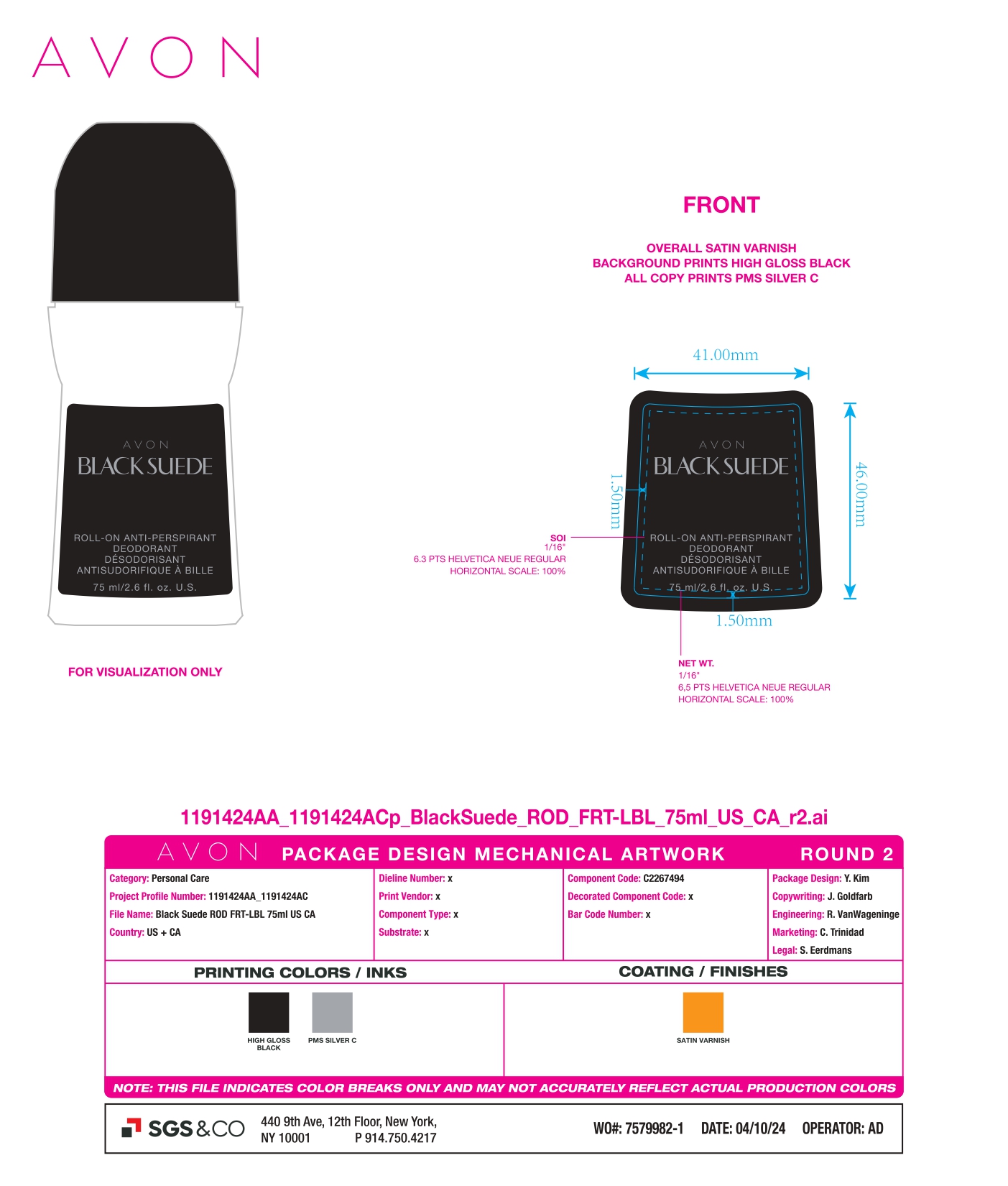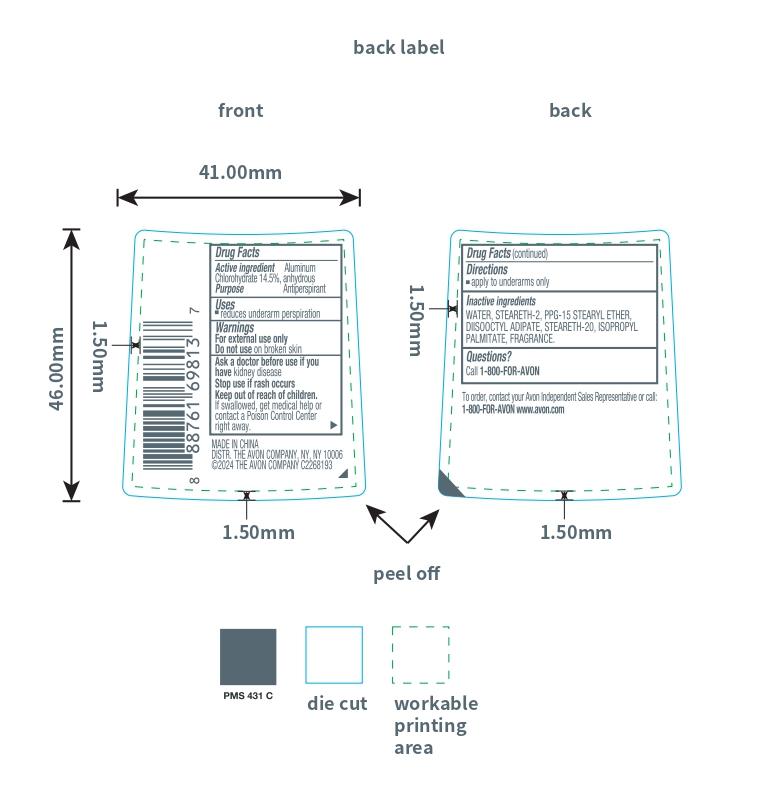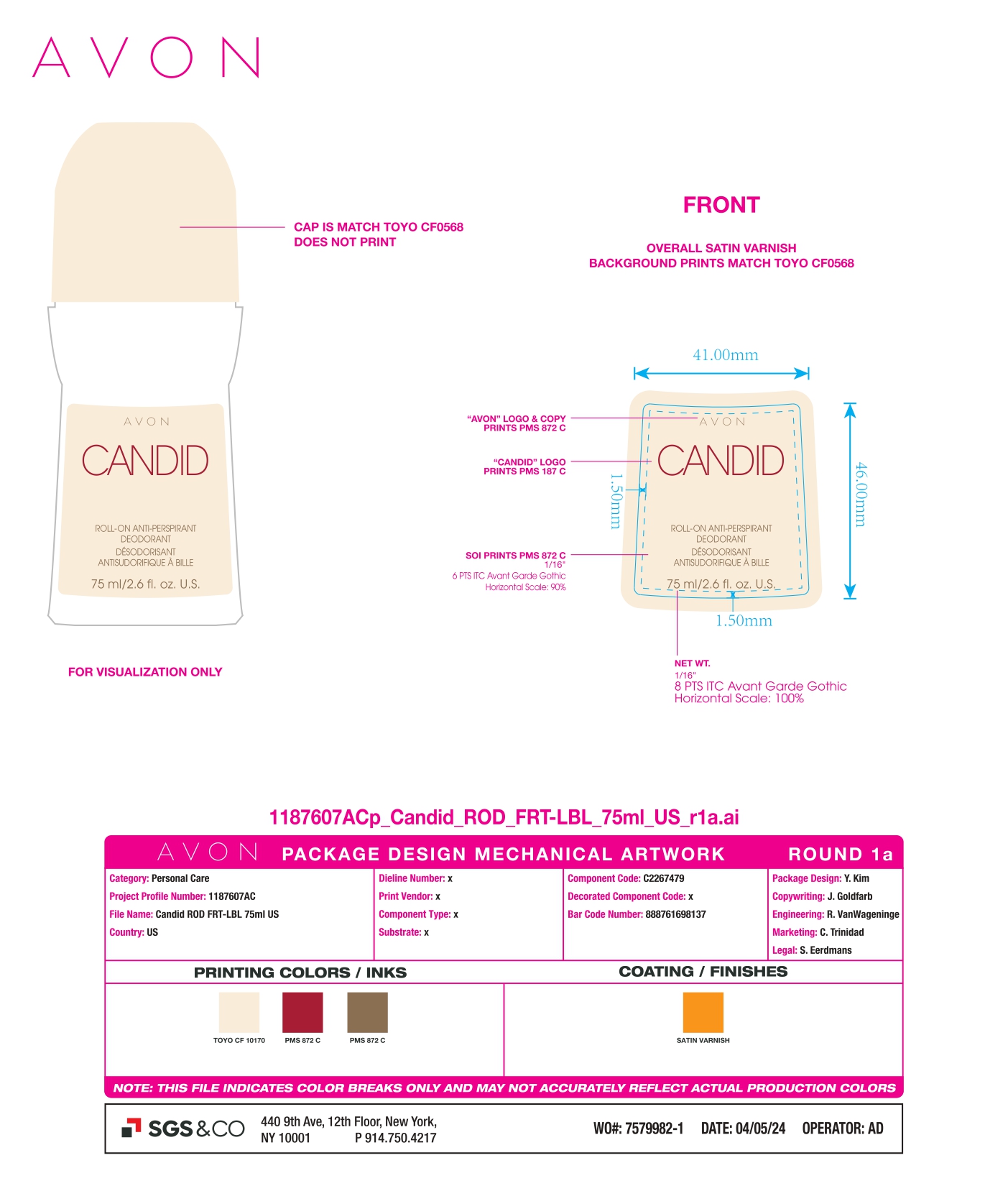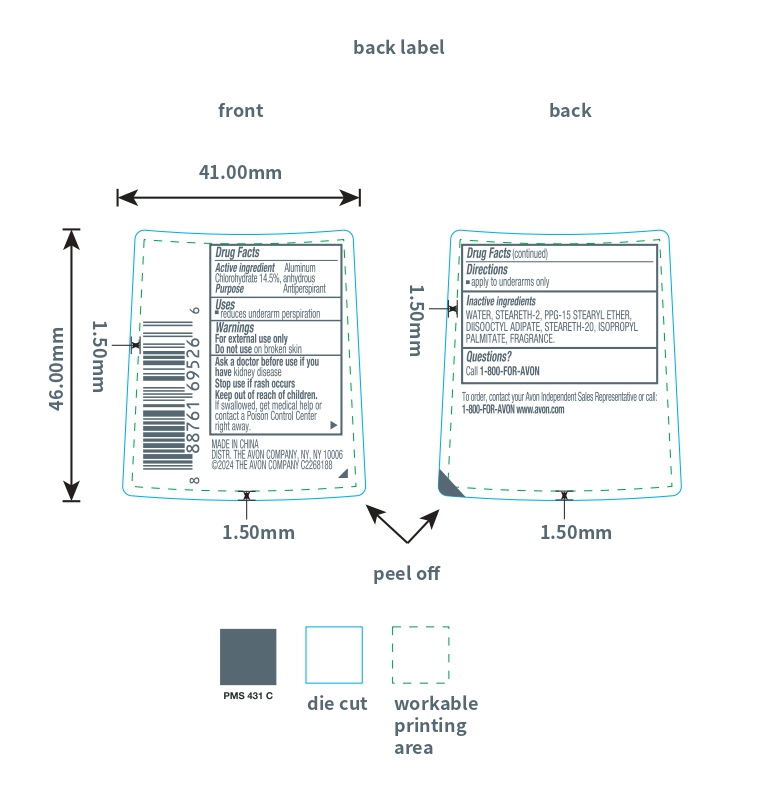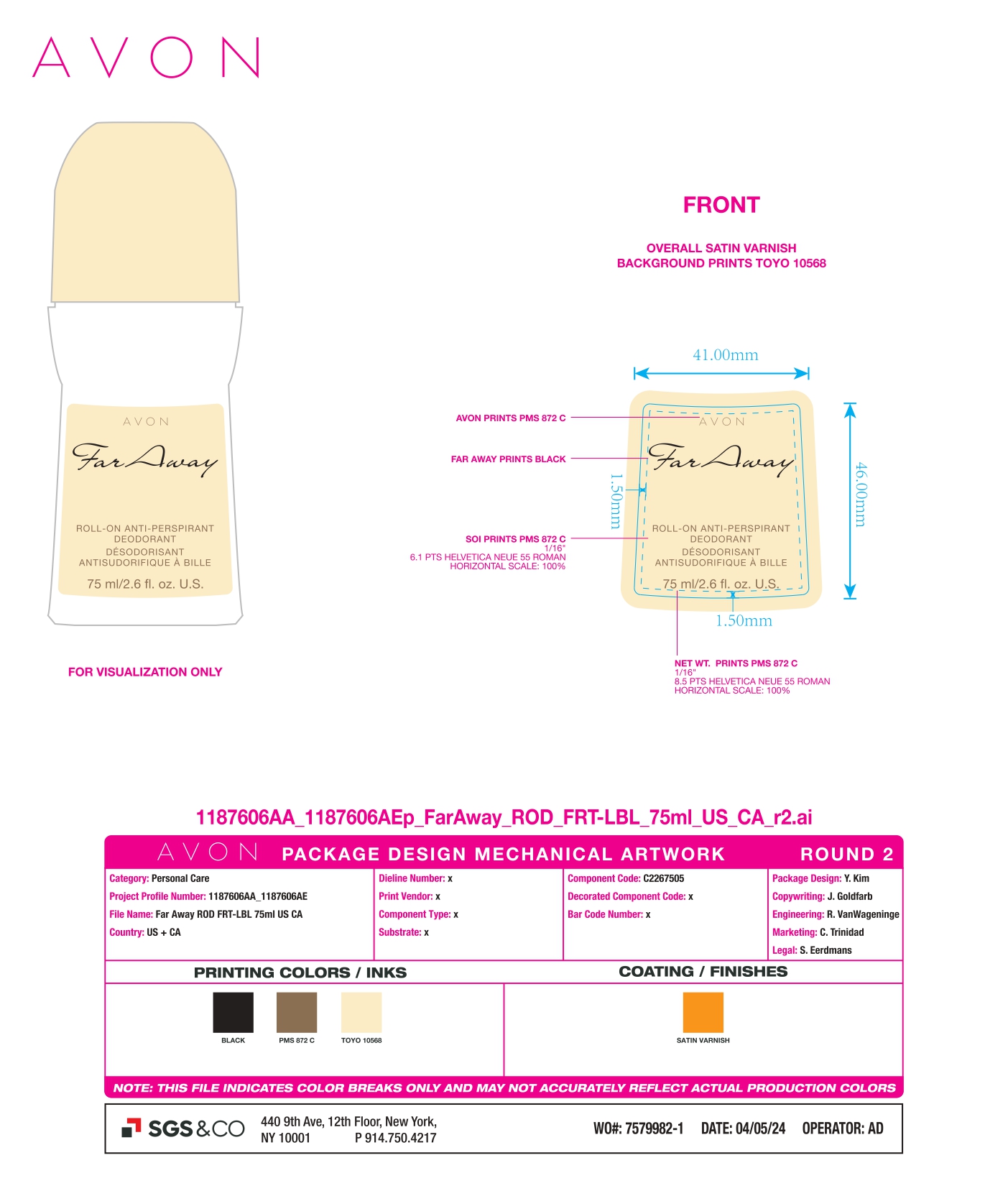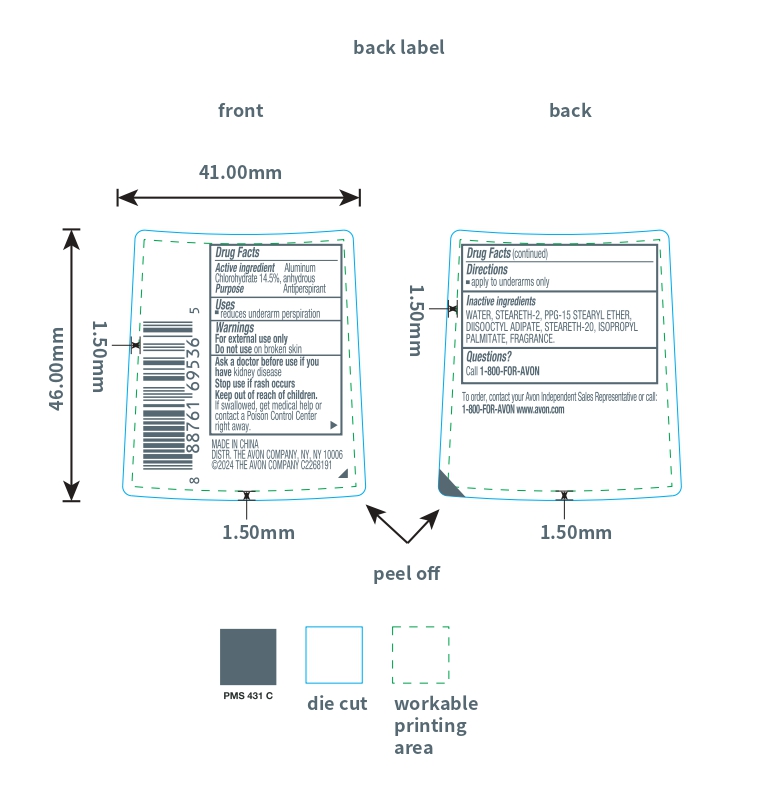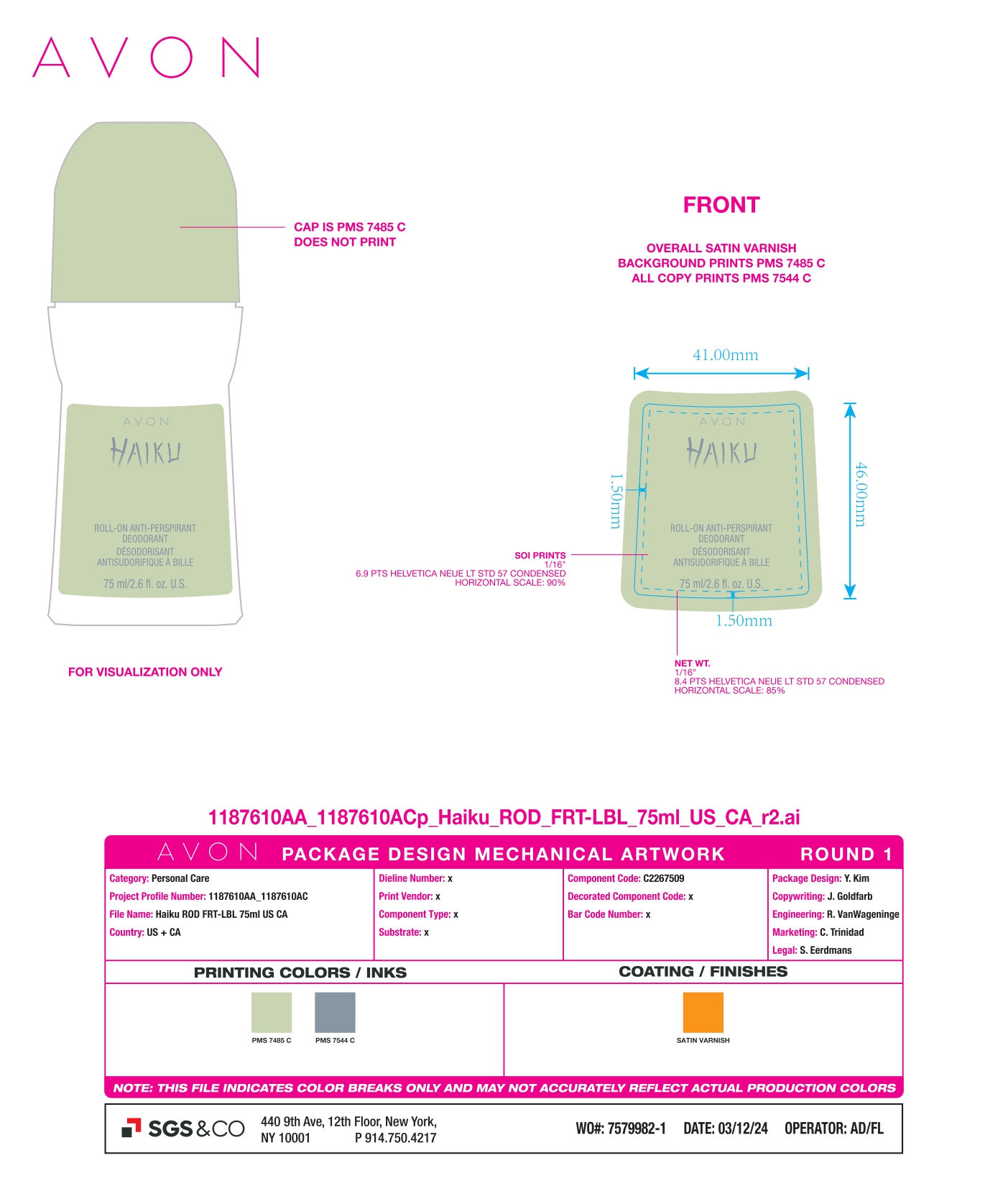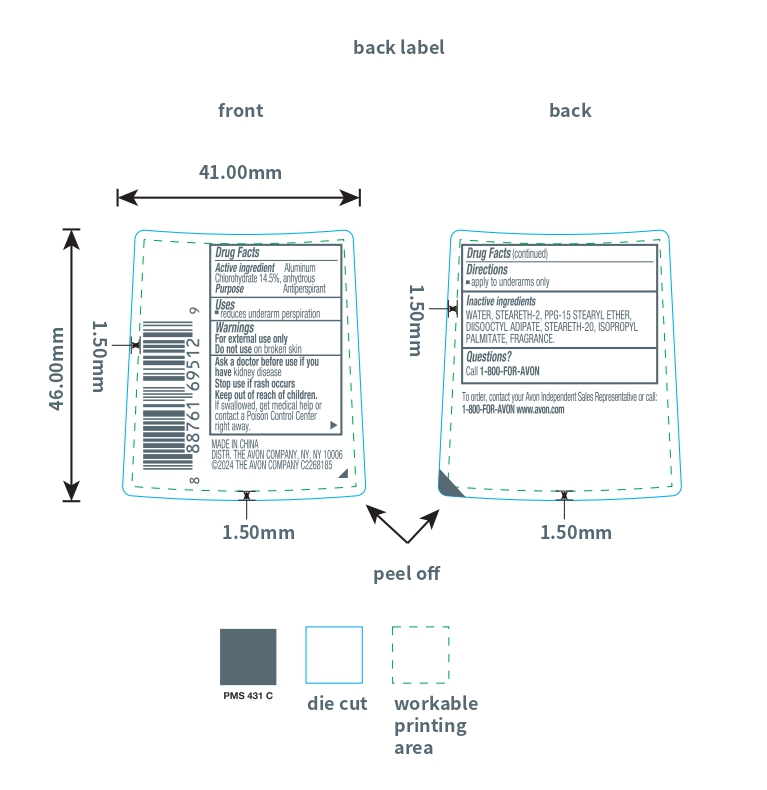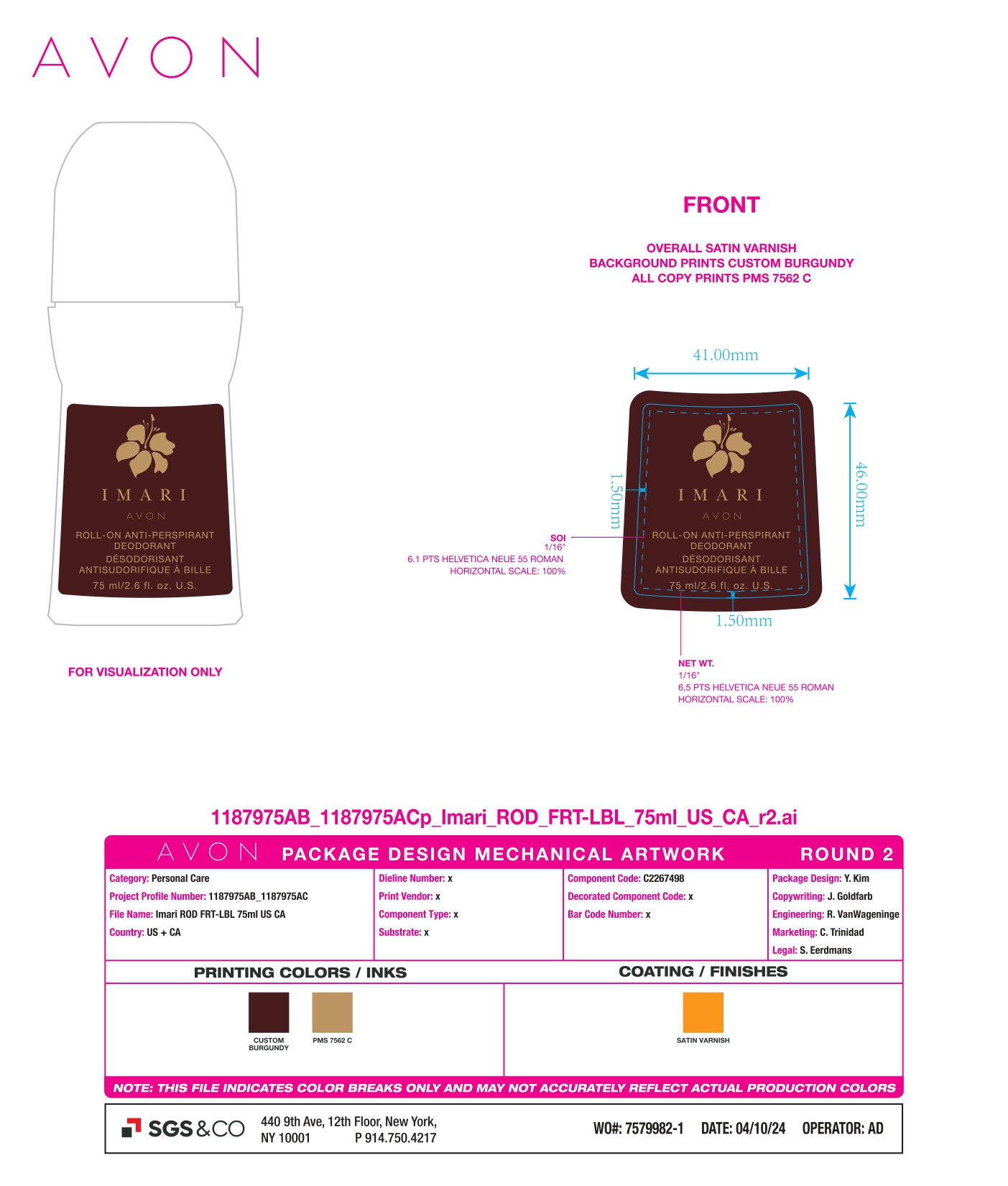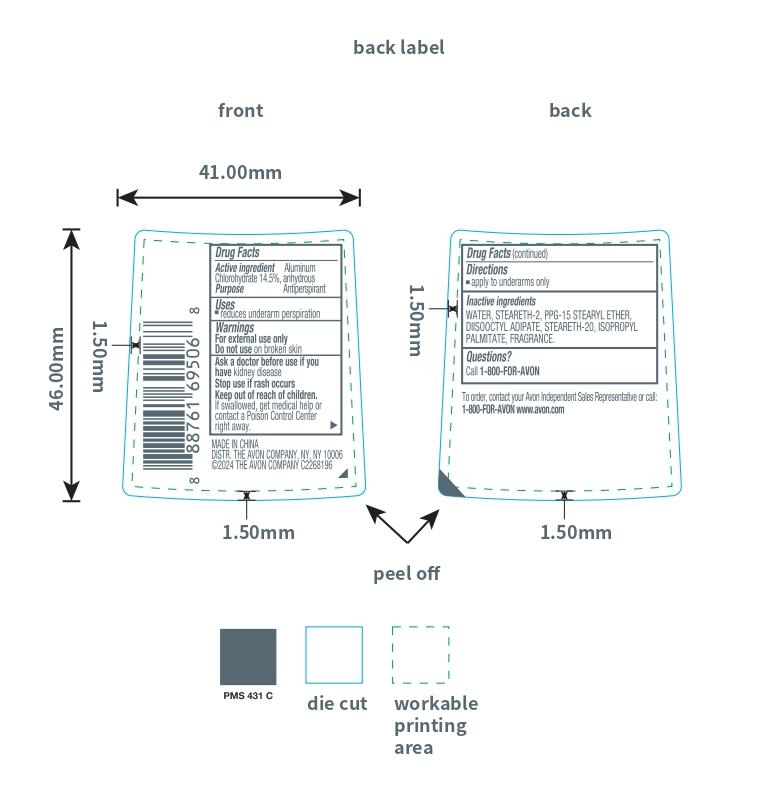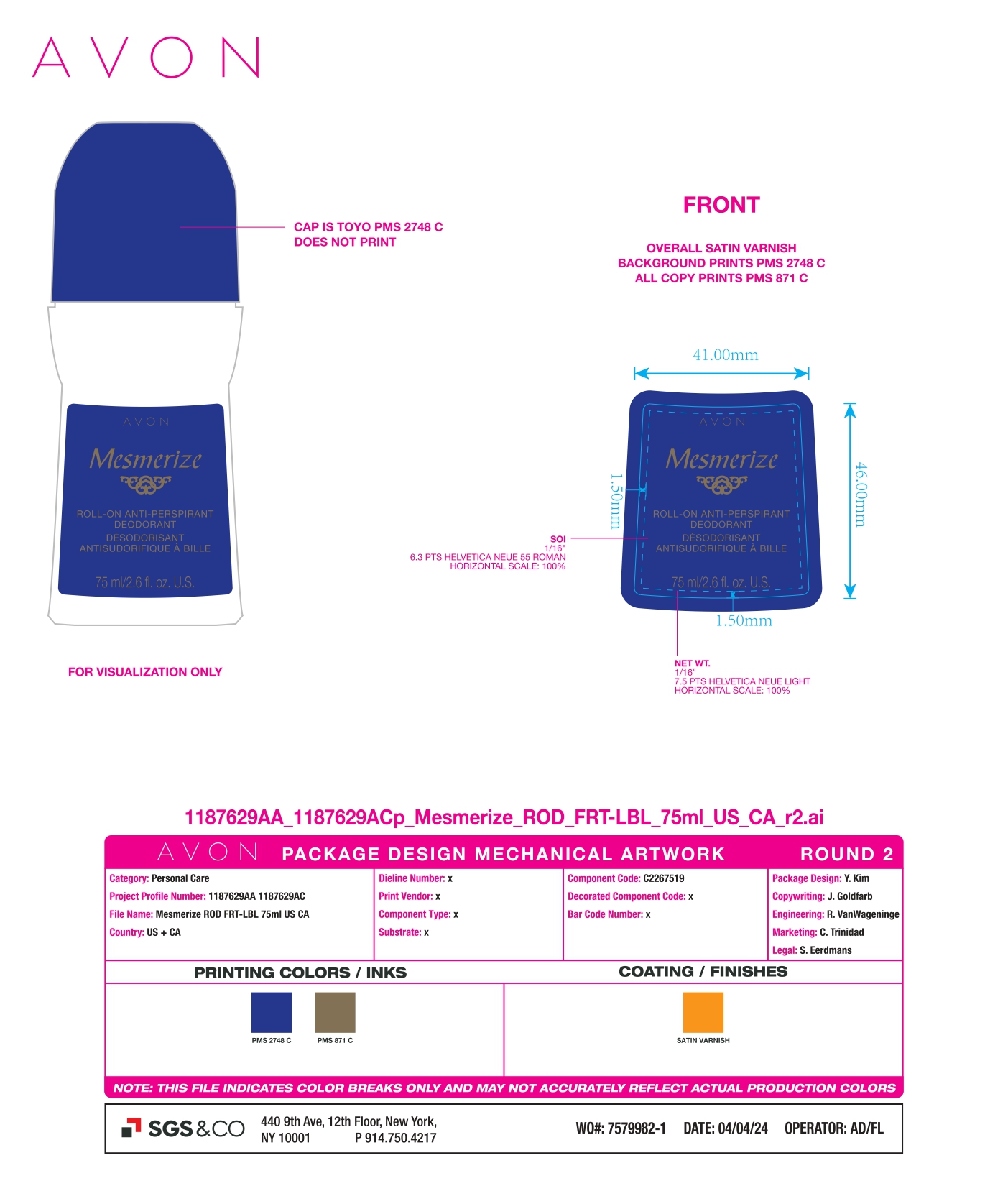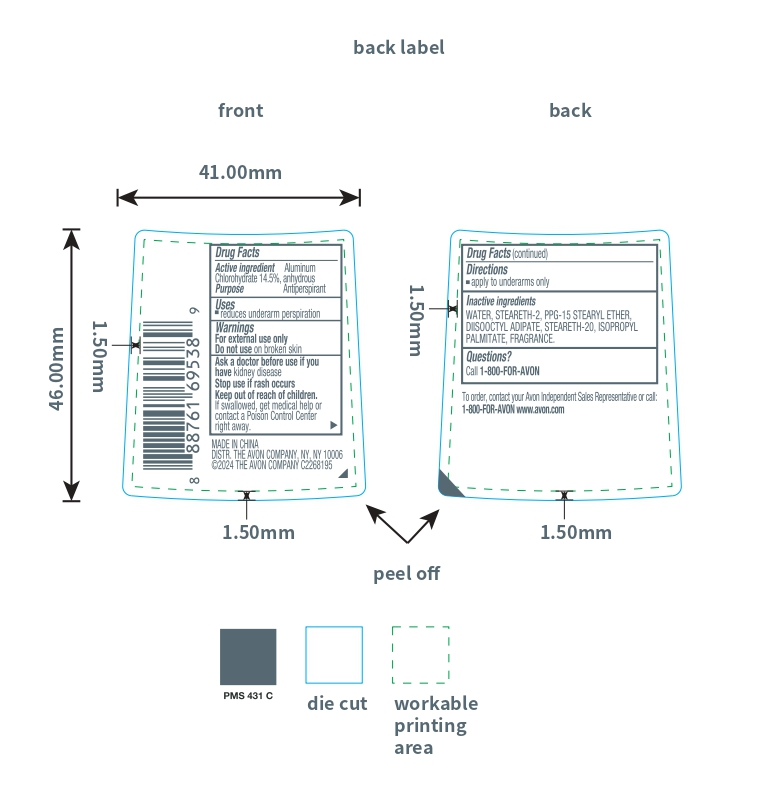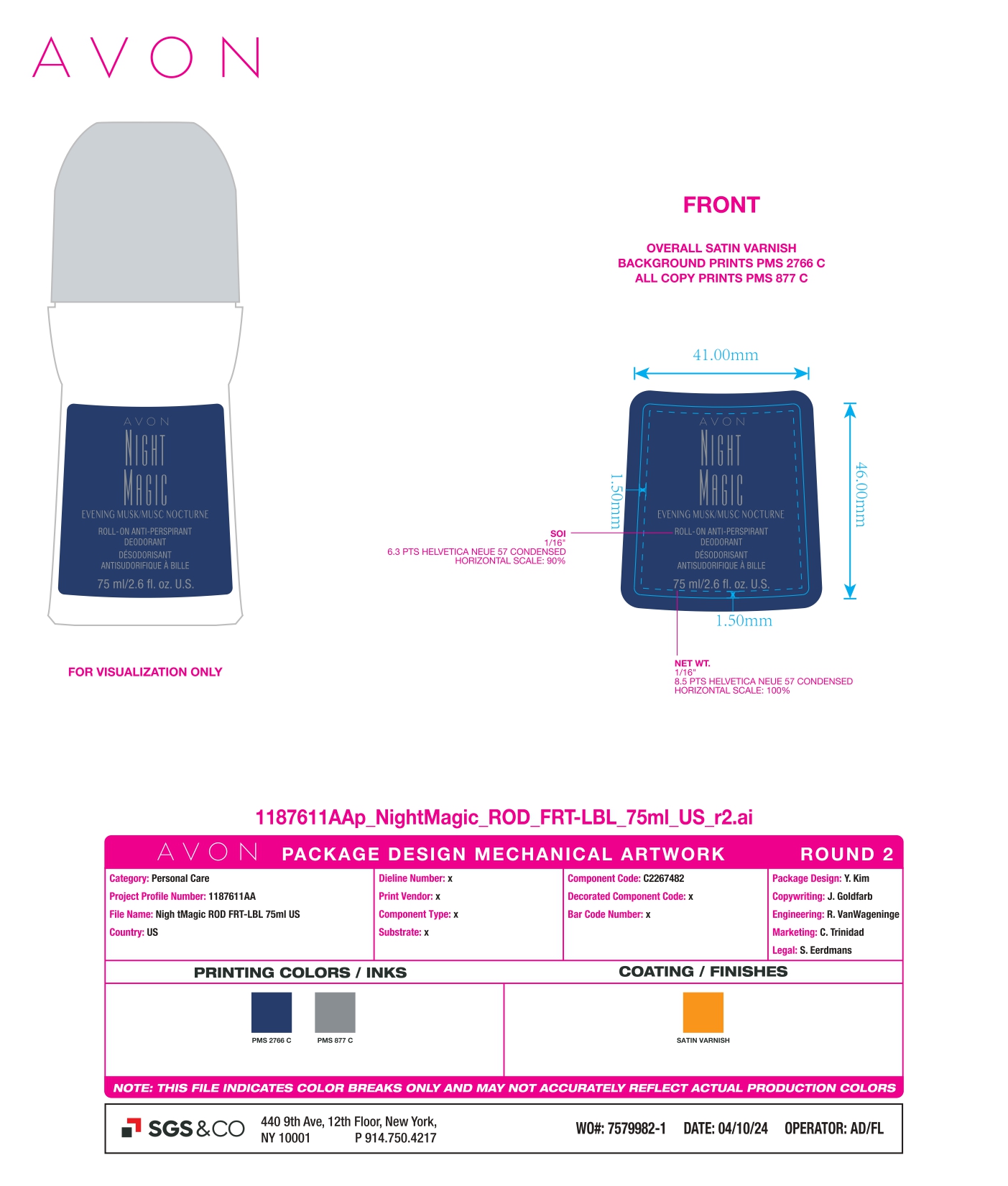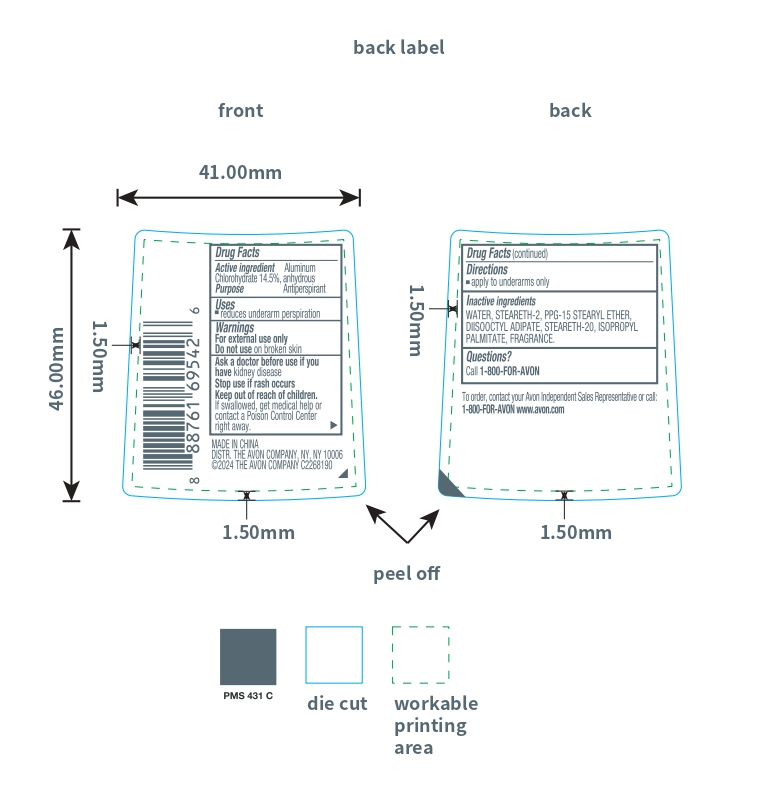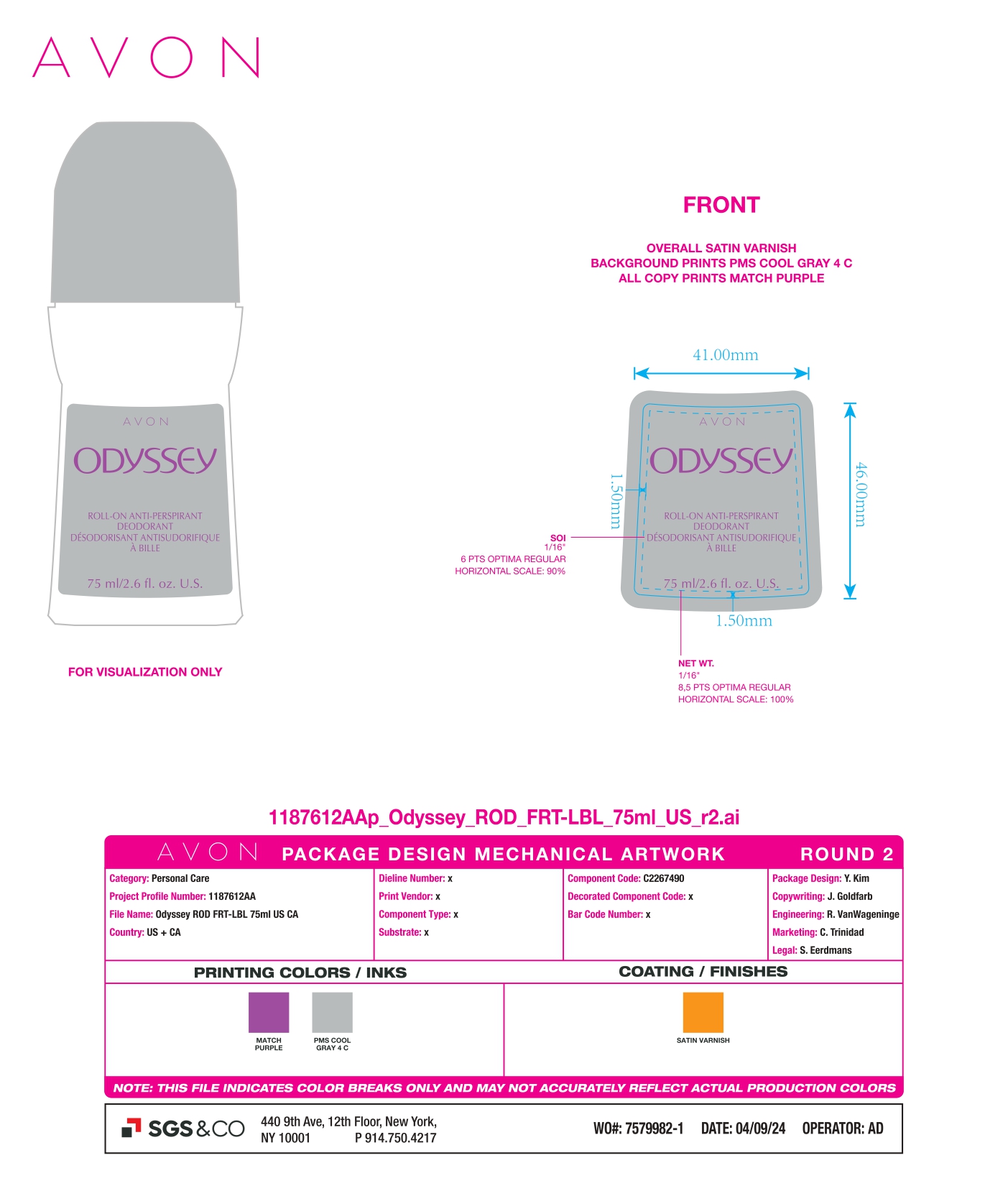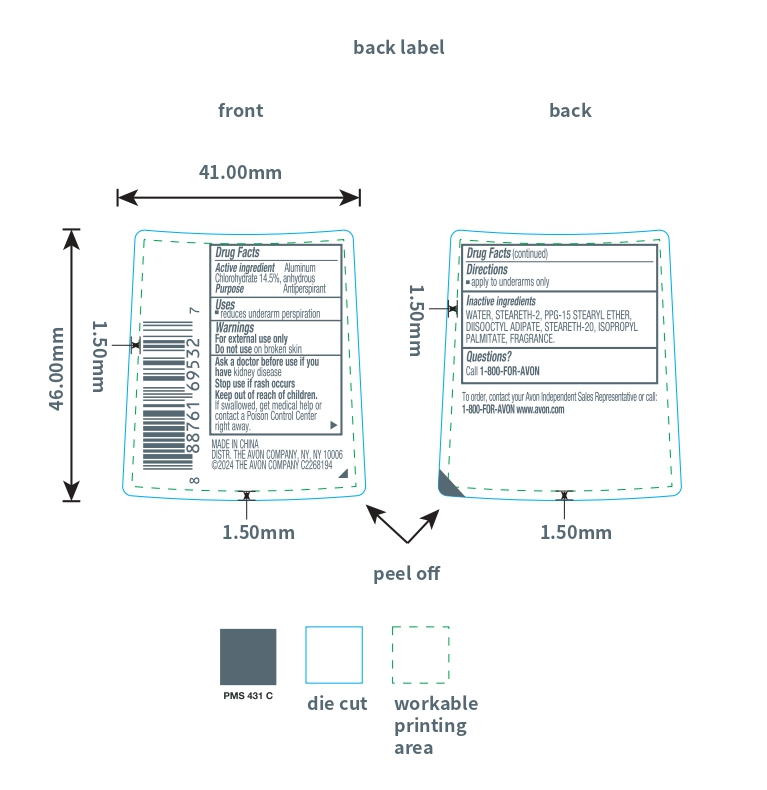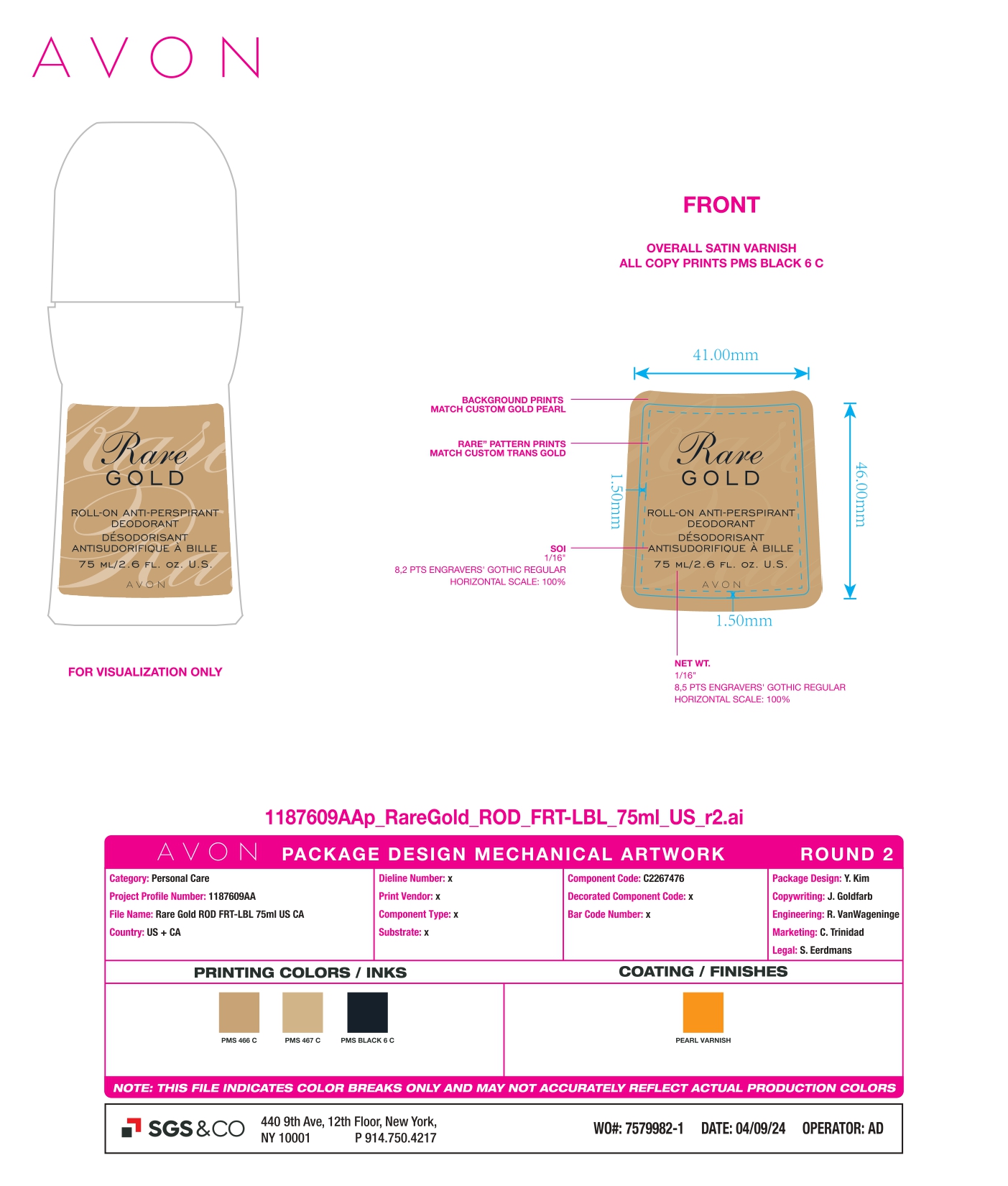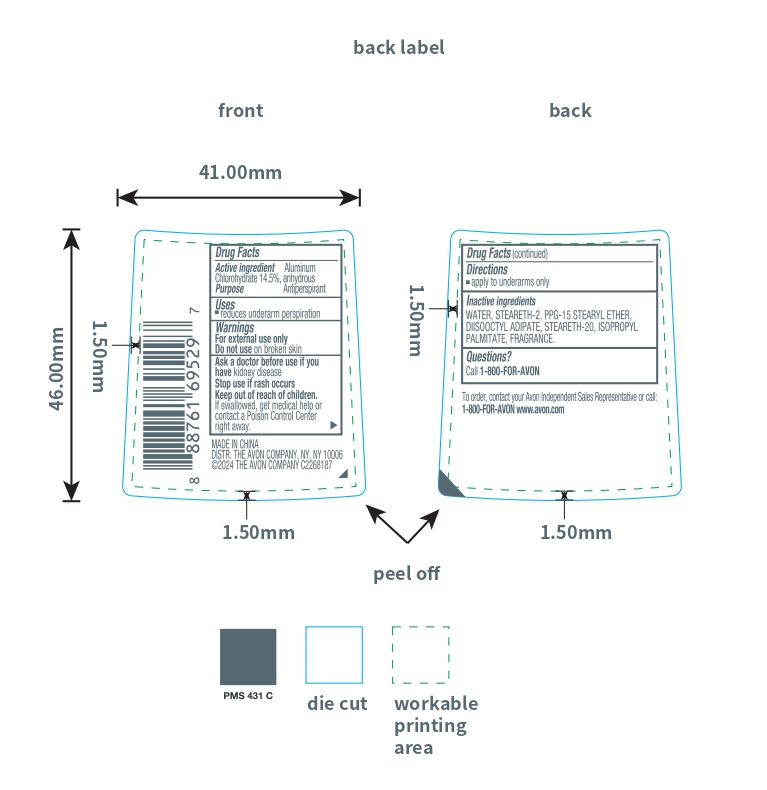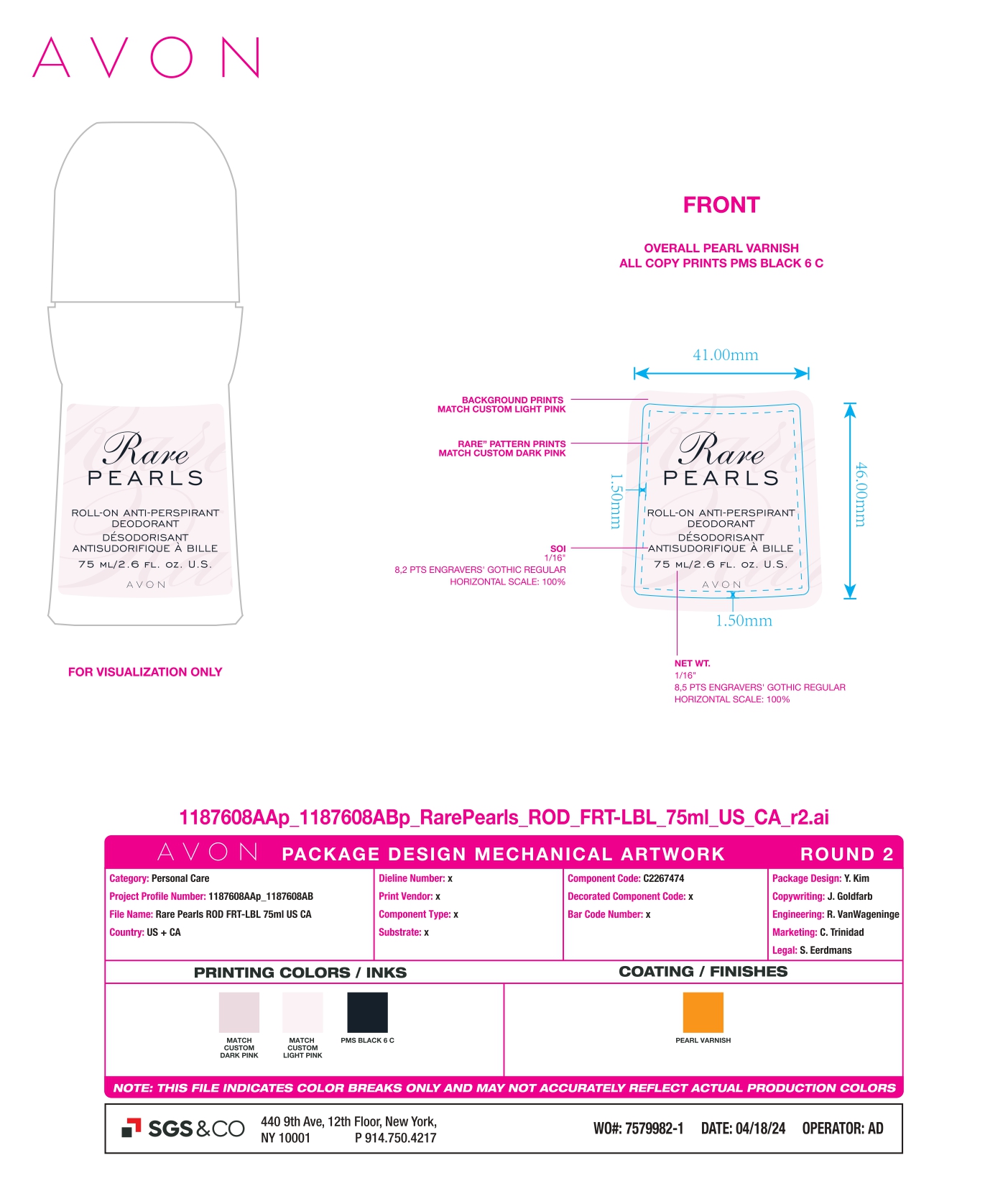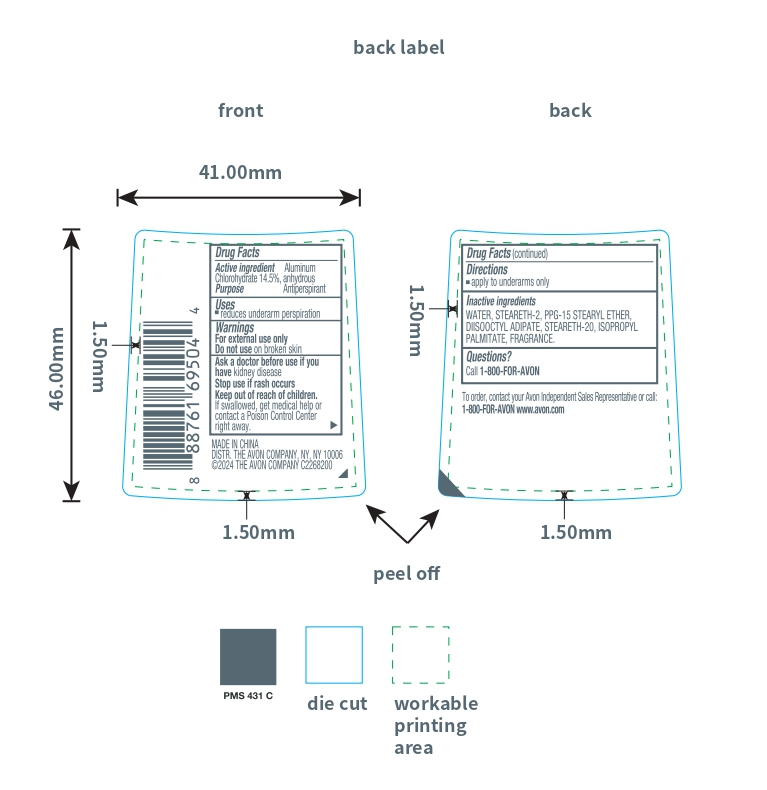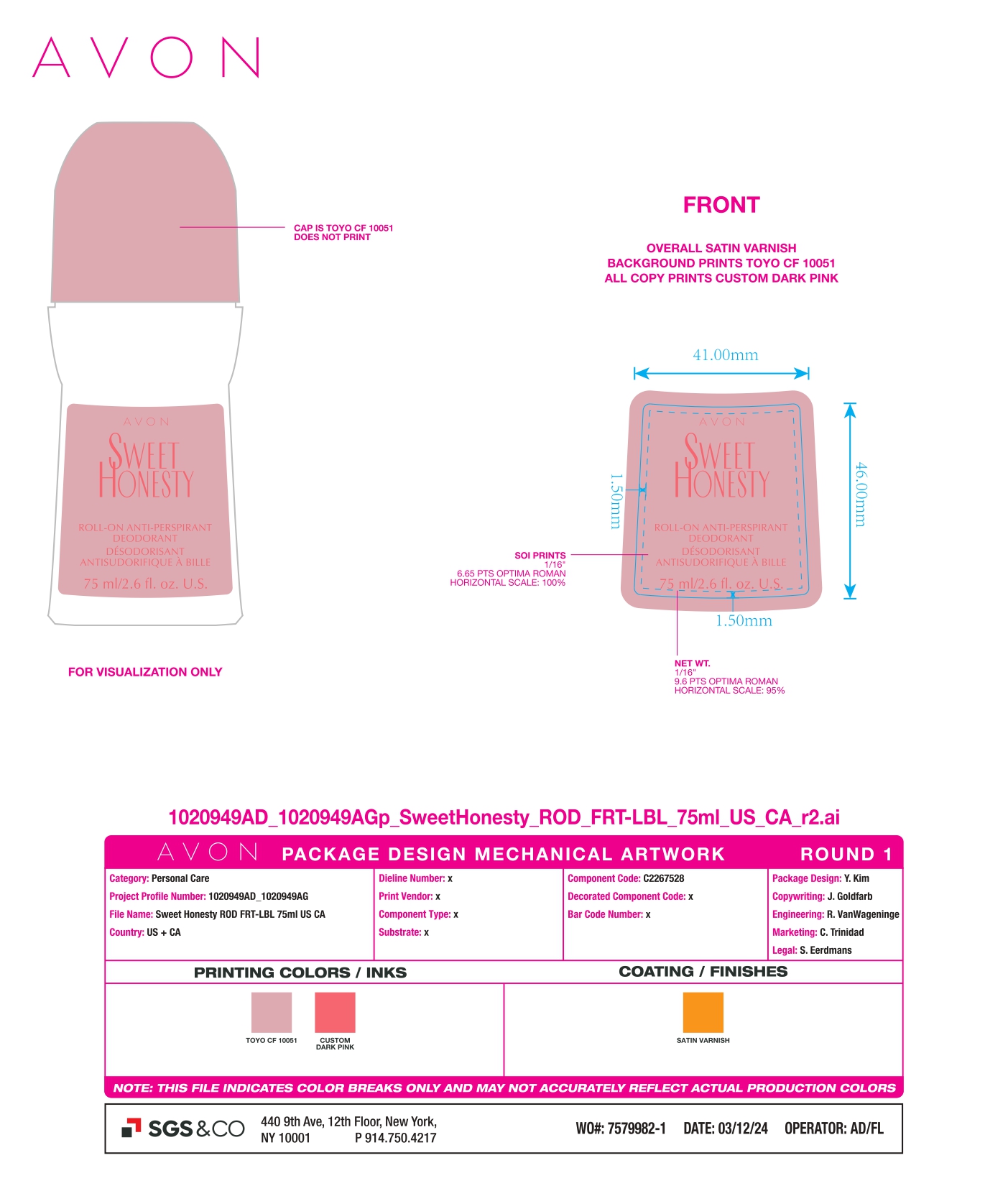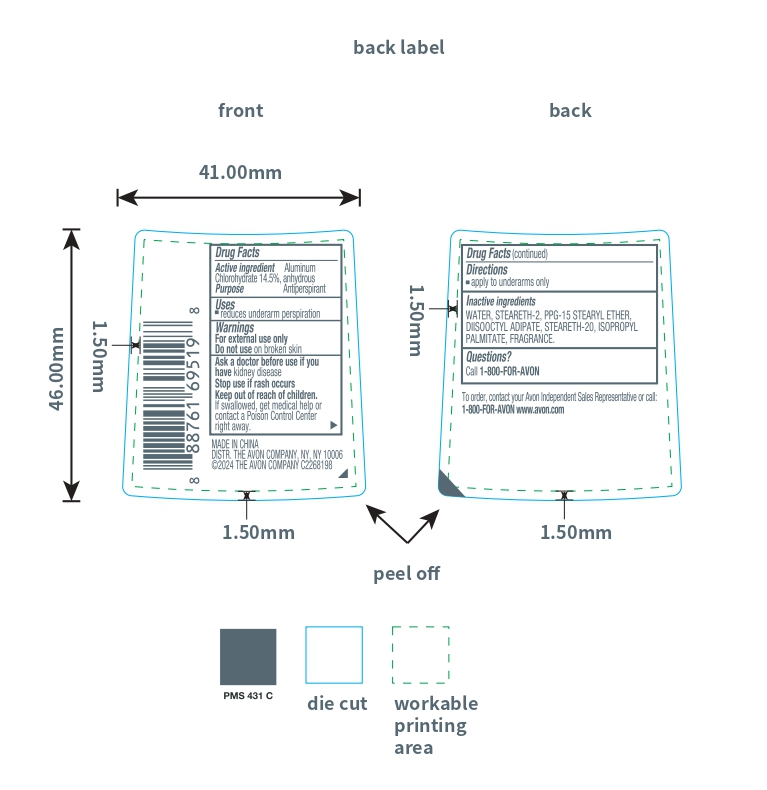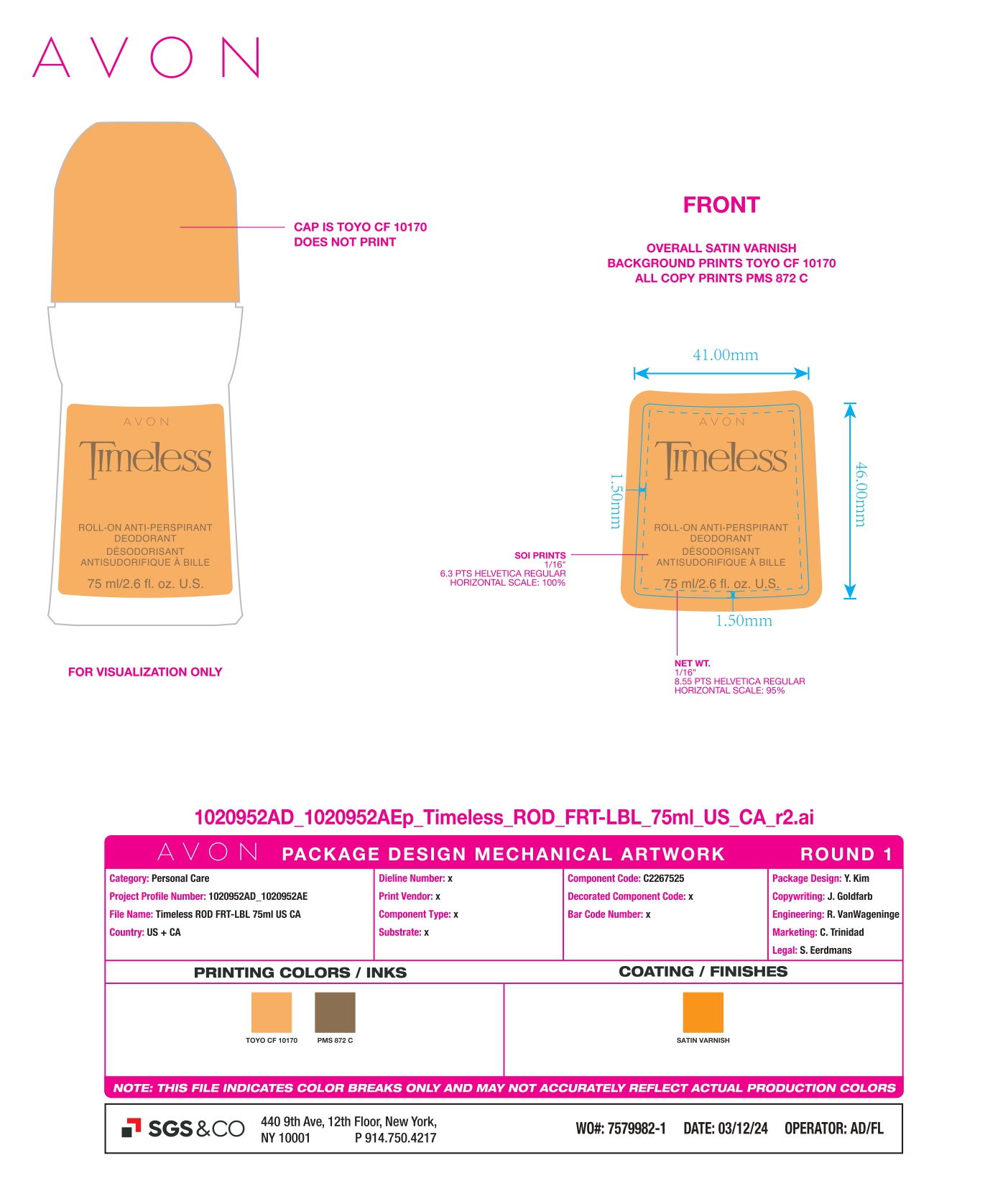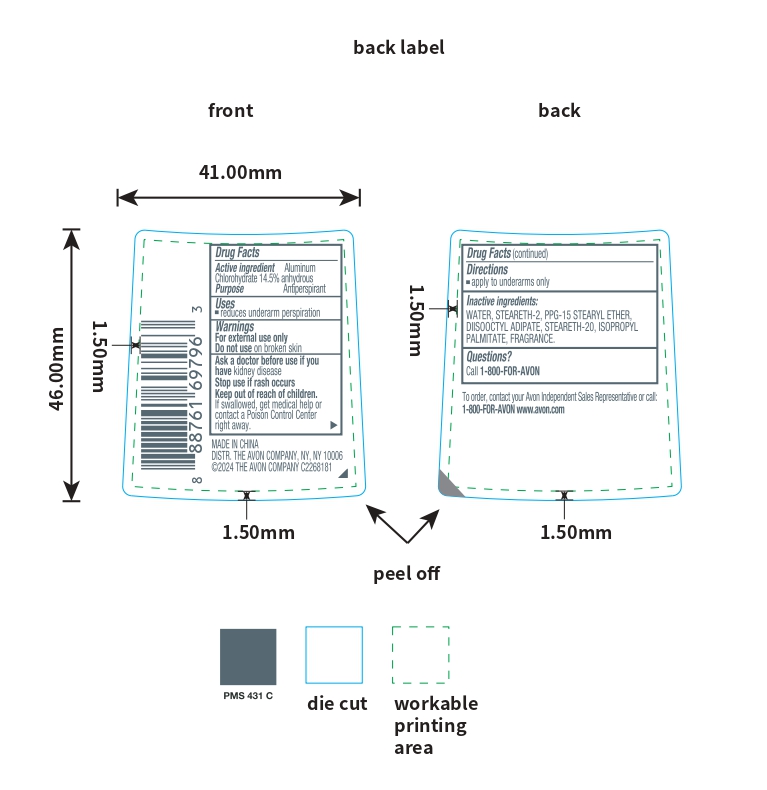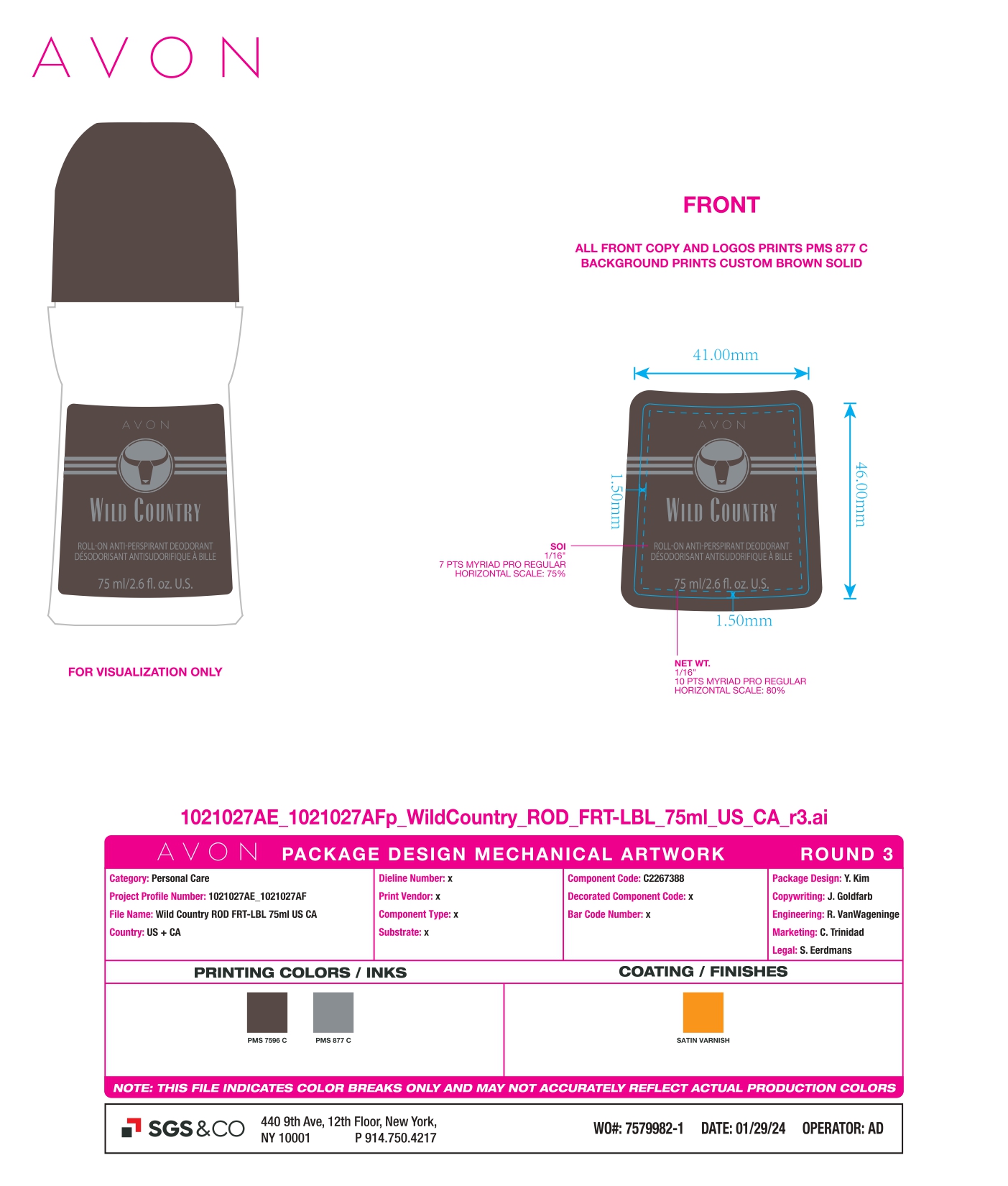 DRUG LABEL: AVON CANDID ROLL-ON ANTI-PERSPIRANT DEODORANT
NDC: 10096-3975 | Form: STICK
Manufacturer: THE AVON COMPANY
Category: otc | Type: HUMAN OTC DRUG LABEL
Date: 20250211

ACTIVE INGREDIENTS: ALUMINUM CHLOROHYDRATE 145 mg/1 mL
INACTIVE INGREDIENTS: ISOPROPYL PALMITATE; WATER; STEARETH-20; PPG-15 STEARYL ETHER; DIISOOCTYL ADIPATE; STEARETH-2

Active Ingredient

Aluminum Chlorohydrate 14.5%

Purpose

Antiperspirant

Uses

Reduces underam perspiration

Warnings

For external use only

Do not use on broke skin

Ask a doctor before use if you have kidney disease

Stop use

Stop use if rash occurs

Keep out of reach of children

DOSAGE AND ADMINISTRATION

If swallowed, get medical help or contact a Poison Control Center right away.

Directions

Apply to underarms only

Inactive Ingredients

WATER, STEARETH-2, PPG-15 STEARYL ETHER, DIISOOCTYL ADIPATE, STEARETH-20, ISOPROYL PALMITATE, FRAGRANCE.

Questions?

Call 1-800-FOR-AVON

MADE IN CHINA

DISTR.THE AVON COMPANY, NY, NY 10006

©2024 THE AVON COMPANY C2268193

To order, contact your Avon Independent Sales Representative or call: 1-800-FOR-AVON www.avon.com